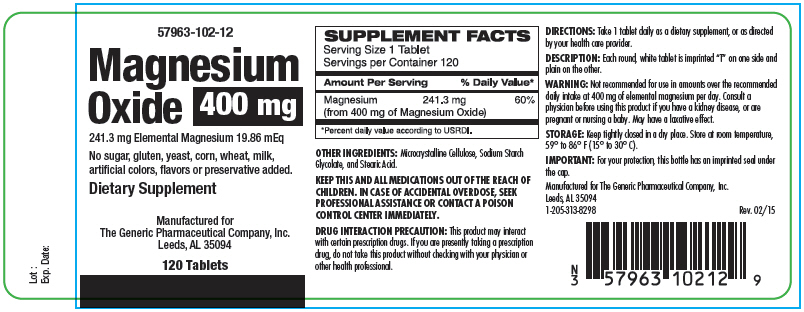 DRUG LABEL: Magnesium Oxide
NDC: 57963-102 | Form: TABLET
Manufacturer: The Generic Pharmaceutical Company
Category: other | Type: DIETARY SUPPLEMENT
Date: 20170111

ACTIVE INGREDIENTS: Magnesium Oxide 400 mg/1 1
INACTIVE INGREDIENTS: Microcrystalline Cellulose; Sodium Starch Glycolate Type A Potato; Stearic Acid

Magnesium Oxide

STATEMENT OF IDENTITY

SUPPLEMENT FACTS

Serving Size 1 Tablet

Servings per Container 120

Amount Per Serving

% Daily Value [Percent daily value according to USRDI.]

Magnesium

241.3 mg

60%

(from 400 mg of Magnesium Oxide)

OTHER INGREDIENTS

Microcrystalline Cellulose, Sodium Starch Glycolate, and Stearic Acid.

WARNINGS

KEEP THIS AND ALL MEDICATIONS OUT OF THE REACH OF CHILDREN. IN CASE OF ACCIDENTAL OVERDOSE, SEEK PROFESSIONAL ASSISTANCE OR CONTACT A POISON CONTROL CENTER IMMEDIATELY.

DRUG INTERACTION PRECAUTION

This product may interact with certain prescription drugs. If you are presently taking a prescription drug, do not take this product without checking with your physician or other health professional.

DIRECTIONS

Take 1 tablet daily as a dietary supplement, or as directed by your health care provider.

DESCRIPTION

Each round, white tablet is imprinted "T" on one side and plain on the other.

WARNING

Not recommended for use in amounts over the recommended daily intake at 400 mg of elemental magnesium per day. Consult a physician before using this product if you have a kidney disease, or are pregnant or nursing a baby. May have a laxative effect.

STORAGE

Keep tightly closed in a dry place. Store at room temperature, 59° to 86° F (15° to 30° C).

IMPORTANT

For your protection, this bottle has an imprinted seal under the cap.

HEALTH CLAIM

Manufactured for The Generic Pharmaceutical Company, Inc.
Leeds, AL 35094
1-205-313-8298

Rev. 02/15

PRINCIPAL DISPLAY PANEL - 400 mg Tablet Bottle Label

57963-102-12

Magnesium
Oxide
400 mg

241.3 mg Elemental Magnesium 19.86 mEq

No sugar, gluten, yeast, corn, wheat, milk,
artificial colors, flavors or preservative added.

Dietary Supplement

Manufactured for
The Generic Pharmaceutical Company, Inc.
Leeds, AL 35094

120 Tablets